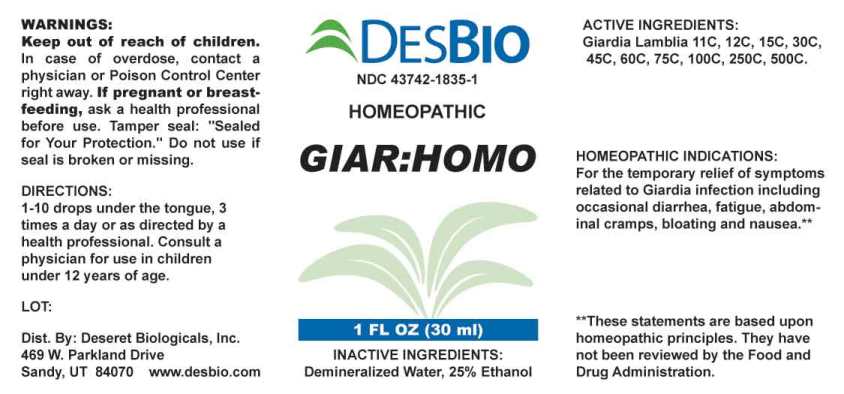 DRUG LABEL: GIAR HOMO
NDC: 43742-1835 | Form: LIQUID
Manufacturer: Deseret Biologicals, Inc
Category: homeopathic | Type: HUMAN OTC DRUG LABEL
Date: 20240923

ACTIVE INGREDIENTS: GIARDIA LAMBLIA 11 [hp_C]/1 mL
INACTIVE INGREDIENTS: WATER; ALCOHOL

DRUG FACTS:

ACTIVE INGREDIENT:

GIARDIA LAMBLIA 11C, 12C, 15C, 30C, 45C, 60C, 75C, 100C, 250C, 500C

HOMEOPATHIC INDICATIONS:

For temporary relief of symptoms related to Giardia infection including occasional diarrhea, fatigue, abdominal cramps, bloating and nausea.**

**These statements are based upon traditional homeopathic principles. They have not been reviewed by the Food and Drug Administration.

WARNINGS:

Keep out of reach of children. In case of overdose, contact a physician or Poison Control Center right away.

If pregnant or breast-feeding, ask a health professional before use.

Tamper seal: "Sealed for Your Protection." Do not use if seal is broken or missing.

Keep out of reach of children. In case of overdose, contact a physician or Poison Control Center right away.

DIRECTIONS:

1-10 drops under the tongue, 3 times a day or as directed by a health professional. Consult a physician for use in children under 12 years of age.

HOMEOPATHIC INDCATIONS:

For temporary relief of symptoms related to Giardia infection including occasional diarrhea, fatigue, abdominal cramps, bloating and nausea.**

**These statements are based upon traditional homeopathic principles. They have not been reviewed by the Food and Drug Administration.

INACTIVE INGREDIENTS:

Demineralized Water, 25% Ethanol

QUESTIONS:

Dist. By: Deseret Biologicals, Inc.

469 Parkland Drive

Sandy, UT 84070 www.desbio.com

PACKAGE LABEL DISPLAY:

DESBIO

NDC 43742-1835-1

HOMEOPATHIC

GIAR:HOMO

1 FL OZ (30 ml)